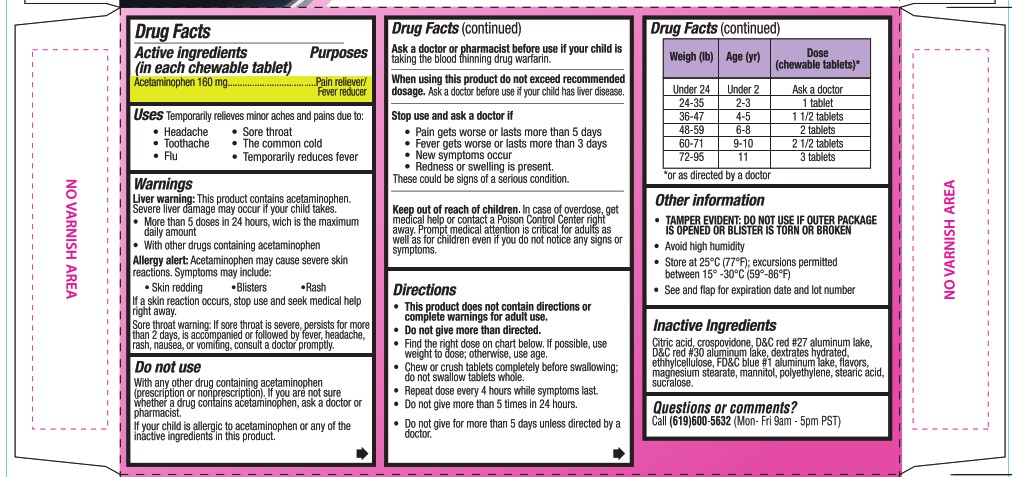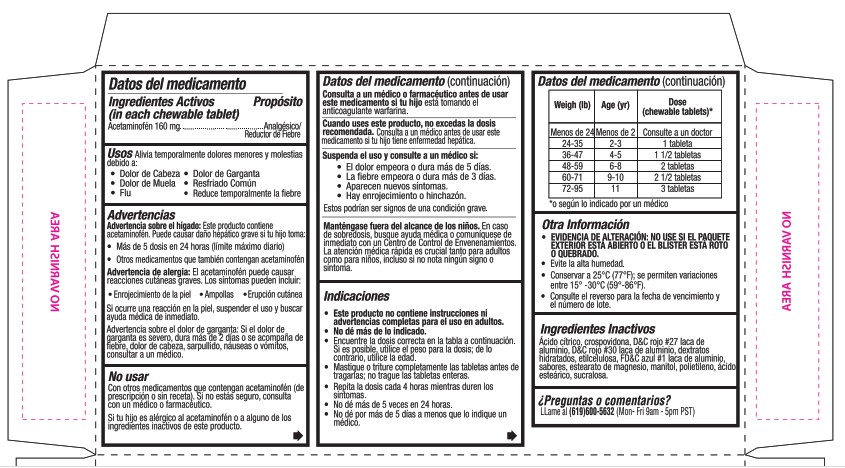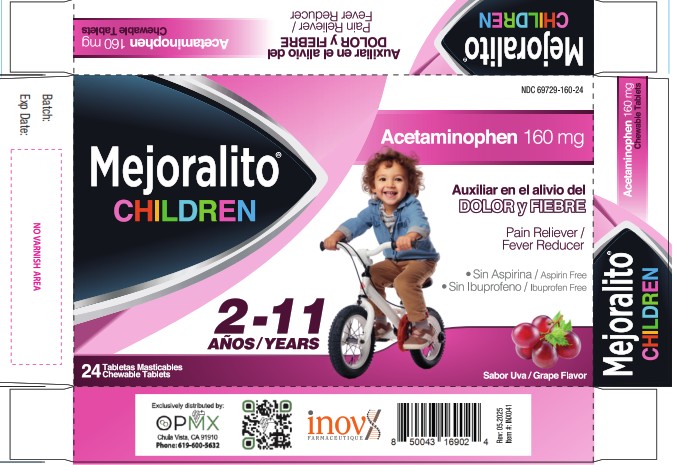 DRUG LABEL: Mejoralito Children
NDC: 69729-160 | Form: TABLET, CHEWABLE
Manufacturer: OPMX LLC
Category: otc | Type: HUMAN OTC DRUG LABEL
Date: 20260130

ACTIVE INGREDIENTS: ACETAMINOPHEN 160 mg/1 1
INACTIVE INGREDIENTS: DEXTRATES; CROSPOVIDONE; MAGNESIUM STEARATE; D&C RED NO. 30 ALUMINUM LAKE; ETHYLCELLULOSE; CITRIC ACID; D&C RED NO. 27 ALUMINUM LAKE; FD&C BLUE NO. 1 ALUMINUM LAKE; POLYETHYLENE; MANNITOL; STEARIC ACID; SUCRALOSE

Mejoralito chewable CHILDREN

Drug Facts

Active ingredients (in each chewable tablet)

Acteaminophen 160 mg

Purposes

Pain reliever/Fever reducer

Uses

Temporarily relieves minor aches and pains due to:

- Headache
- Toothache
- Flu
- Sore throat
- The common cold
- Temporarily reduces fever

Warnings

Liver warning: This product contains acetaminophen.

Severe liver damage may occur if your child takes.

- More than 5 doses in 24 hours, wich is the maximum daily amount
- With other drugs containing acetaminophen

Allergy alert: Acetaminophen may cause severe skin reactions. Symptoms may include:

- Skin redding
- Blisters
- Rash

If a skin reaction occurs, stop use and seek medical help right away.

Sore throat warning: If sore throat is severe, persists for more than 2 days, is accompanied or followed by fever, headache, rash, nausea, or vomiting, consult a doctor promptly.

Do not use

With any other drug containing acetaminophen (prescription or nonprescription). If yu are not sure whether a drug contains acetaminophen, ask a doctor or a pharmacist.

If your child is allergic to acetaminophen or any of the inactive ingredients in this product.

Ask a doctor or pharmacist before use if your child is

taking the blood thinning drug warfarin.

When using this product do not exceed recommended dosage.

Ask a doctor before use if your child has liver disease.

Stop use and ask a doctor if

- Pain gets worse or lasts more than 5 days
- Fever gets worse or lasts more than 3 days
- New symptoms occur
- Redness or swelling is present.

These could be signs of a serious condition.

Keep out of reach of children.

OVERDOSAGE

In case of overdose, get medical help or contact a Poison Control Center right away. Prompt medical attention is critical for adults as well as for children even if you do not notice any signs or symptoms.

Directions

- This product does not contain directions or complete warnings for adult use.
- Do not give more than directed.
- Find the right dose on chart below. If possible, use weight to dose; otherwise, use age.
- Chew or crush tablets completly before swallowing; do not swallow tablets whole.
- Repeat dose every 4 hours while symptoms last.
- Do not give more than 5 times in 24 hours.
- Do not give for more than 5 days unless directed by a doctor.

Weigh (lb) | Age (yr) | Dose (chewable tablets)*
Under 24 | Under 2 | Ask a doctor
24-35 | 2-3 | 1 tablet
36-47 | 4-5 | 1 1/2 tablets
48-59 | 6-8 | 2 tablets
60-71 | 9-10 | 2 1/2 tablets
72-95 | 11 | 3 tablets

*or as directed by a doctor

Other information

- TAMPER EVIDENT: DO NOT USE IF OUTER PACKAGE IS OPENED OR BLISTER IS TORN OR BROKEN
- Avoid high humidity
- Store at 25°C (77°F); excursions permitted between 15° -30°C (59° -86°F)
- See and flap for expiration date and lot number

Inactive Ingredients

Citric acid, crospovidone, D&C red #27 aluminum lake, D&C red #30 aluminium lake, dextrates hydrated, ethylcellulose, FD&C blue #1 aluminum lake, flavors, magnesium stearate, mannitol, polyethylene, stearic acid, sucralose.

Questions or comments?

Call (619)600-5632 (Mon- Fri 9am - 5pm PST)

Exclusively distributed by:

OPMX
Chula Vista, CA 91910

Phone: 619-600-5632

inov

FARMACEUTIQUE

PRINCIPAL DISPLAY PANEL

NDC 69729-160-24

Mejoralito®

CHILDREN

Acetaminophen 160 mg

Auxiliar en el alivio del
DOLOR y FIEBRE

Pain reliever/

Fever Reducer

- Sin Aspirina / Aspirin Free
- Sin Ibuprofeno / Ibuprofen Free

2-11 AÑOS/YEARS

24 Tabletas Masticables

Chewable Tablets

Sabor Uva/Grape Flavor